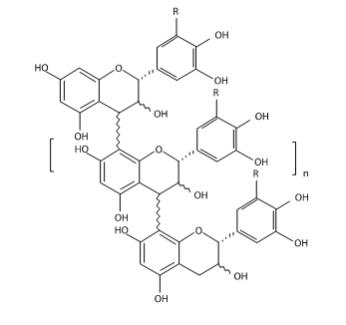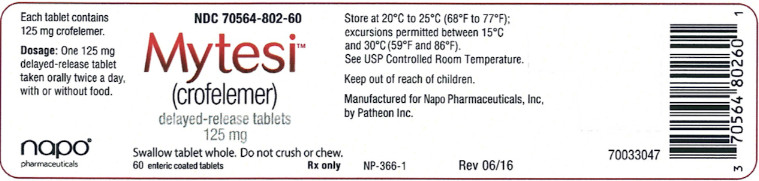 DRUG LABEL: MYTESI
NDC: 70564-802 | Form: TABLET, COATED
Manufacturer: Napo Pharmaceuticals, Inc.
Category: prescription | Type: HUMAN PRESCRIPTION DRUG LABEL
Date: 20251222

ACTIVE INGREDIENTS: CROFELEMER 125 mg/1 1
INACTIVE INGREDIENTS: CELLULOSE, MICROCRYSTALLINE; CROSCARMELLOSE SODIUM; SILICON DIOXIDE; MAGNESIUM STEARATE; ETHYL ACRYLATE; TALC; TRIETHYL CITRATE; XANTHAN GUM; TITANIUM DIOXIDE; PROPYLPARABEN; METHYLPARABEN

HIGHLIGHTS OF PRESCRIBING INFORMATION

These highlights do not include all the information needed to use MYTESI safely and effectively. See full prescribing information for MYTESI.
MYTESI® (crofelemer) delayed-release tablets for oral use
Initial U.S. Approval: 2012

1 INDICATIONS AND USAGE

MYTESI is an anti-diarrheal indicated for the symptomatic relief of non-infectious diarrhea in adult patients with HIV/AIDS on anti-retroviral therapy. (1)

2 DOSAGE AND ADMINISTRATION

- Before starting MYTESI, rule out infectious etiologies of diarrhea. (2, 5.1)
- The recommended adult dosage is 125 mg taken orally twice a day, with or without food. (2)
- Do not crush or chew the tablets. Swallow whole. (2)

3 DOSAGE FORMS AND STRENGTHS

Delayed-Release Tablets: 125 mg (3)

4 CONTRAINDICATIONS

None (4)

5 WARNINGS AND PRECAUTIONS

Risks of Treatment in Patients with Infectious Diarrhea: Consider infectious etiologies of diarrhea before starting treatment to reduce the risk of inappropriate therapy and worsening disease. (2, 5.1)

6 ADVERSE REACTIONS

Most common adverse reactions (≥ 3%) are upper respiratory tract infection, bronchitis, cough, flatulence and increased bilirubin. (6.1)

To report SUSPECTED ADVERSE REACTIONS, contact Napo Pharmaceuticals at 1-844-722-8256 or FDA at 1-800-FDA-1088 or www.fda.gov/medwatch.

8 USE IN SPECIFIC POPULATIONS

Lactation: Women infected with HIV-1 should be instructed not to breastfeed due to the potential for HIV transmission. (8.2)

FULL PRESCRIBING INFORMATION

1 INDICATIONS AND USAGE

MYTESI is indicated for symptomatic relief of non-infectious diarrhea in adult patients with HIV/AIDS on anti-retroviral therapy.

2 DOSAGE AND ADMINISTRATION

Before starting MYTESI, rule out infectious etiologies of diarrhea [see Warnings and Precautions (5.1)]. The recommended adult dosage of MYTESI is 125 mg taken orally two times a day, with or without food. Do not crush or chew MYTESI tablets. Swallow whole.

3 DOSAGE FORMS AND STRENGTHS

Delayed-Release Tablets: 125 mg of crofelemer as a white, oval, delayed-release tablet printed on one side with 125SLXP.

4 CONTRAINDICATIONS

None.

5 WARNINGS AND PRECAUTIONS

5. 1 Risks of Treatment in Patients with Infectious Diarrhea

Before starting MYTESI, rule out infectious etiologies of diarrhea. If infectious etiologies are not considered, and MYTESI is initiated based on a presumptive diagnosis of non-infectious diarrhea, then there is a risk that patients with infectious etiologies will not receive the appropriate treatments, and their disease may worsen. MYTESI is not indicated for the treatment of infectious diarrhea.

6 ADVERSE REACTIONS

6.1 Clinical Trials Experience

Because clinical trials are conducted under widely varying conditions, adverse reaction rates observed in the clinical trials of a drug cannot be directly compared to rates in the clinical trials of another drug and may not reflect the rates observed in practice.

A total of 696 HIV-positive patients in three placebo-controlled trials received MYTESI for a mean duration of 78 days. Of the total population across the three trials, 229 patients received a dosage of 125 mg twice a day for a mean duration of 141 days, and 171 patients received one of four higher than recommended dosages for a mean duration of 139 days (N=69) 14 days (N=102), 146 days (N=54), and 14 days (N=242), respectively.

Adverse reactions in patients treated with MYTESI 125 mg twice daily that occurred in at least 2% of patients and at a higher incidence than placebo are provided in Table 1.

Table 1: Common Adverse Reactions [occurring in at least 2% of patients and at a higher incidence than placebo] in HIV-Positive Patients in Three Placebo-Controlled Trials
Adverse Reaction | MYTESI 125 mg Twice Daily N = 229 n (%) | Placebo N = 274 n (%)
Upper respiratory tract infection | 13 (6) | 4 (2)
Bronchitis | 9 (4) | 0
Cough | 8 (4) | 3 (1)
Flatulence | 7 (3) | 3 (1)
Increased bilirubin | 7 (3) | 3 (1)
Nausea | 6 (3) | 4 (2)
Back pain | 6 (3) | 4 (2)
Arthralgia | 6 (3) | 0
Urinary tract infection | 5 (2) | 2 (1)
Nasopharyngitis | 5 (2) | 2 (1)
Musculoskeletal pain | 5 (2) | 1 (<1)
Hemorrhoids | 5 (2) | 0
Giardiasis | 5 (2) | 0
Anxiety | 5 (2) | 1 (<1)
Increased alanine aminotransferase | 5 (2) | 3 (1)
Abdominal distension | 5 (2) | 1 (<)

Less common adverse reactions that occurred in between 1% and 2% of patients taking 125 mg twice daily of MYTESI were abdominal pain, acne, increased aspartate aminotransferase, increased conjugated bilirubin, increased unconjugated blood bilirubin, constipation, depression, dermatitis, dizziness, dry mouth, dyspepsia, gastroenteritis, herpes zoster, nephrolithiasis, pain in extremity, pollakiuria, sinusitis and decreased white blood cell count.

7 DRUG INTERACTIONS

7.1 Nelfinavir, Zidovudine, and Lamivudine

MYTESI administration did not have a clinically relevant interaction with nelfinavir, zidovudine, or lamivudine in a drug-drug interaction trial [see Clinical Pharmacology (12.3)].

8 USE IN SPECIFIC POPULATIONS

8.1 Pregnancy

Risk Summary

Crofelemer is minimally absorbed systemically by the oral route of administration and maternal use is not expected to result in fetal exposure to the drug [see Clinical Pharmacology (12.3)].

In pregnant rats, no adverse fetal effects were observed with oral administration of crofelemer at doses up to 177 times the recommended clinical dose during the period of organogenesis. In pregnant rabbits, an increase in fetal resorptions and abortions compared to controls were observed with crofelemer at a dose of 96 times the recommended clinical dose. However, it is not clear whether these effects in rabbits are related to the maternal toxicity (decreased body weight and decreased food consumption) observed at this dose (see Data).

The estimated background risk of major birth defects and miscarriage for the indicated population is unknown. All pregnancies have a background risk of birth defect, loss, or other adverse outcomes. In the U.S. general population, the estimated background risk of major birth defects and miscarriage in clinically recognized pregnancies is 2 to 4% and 15 to 20%, respectively.

Data

Animal Data

Crofelemer was not teratogenic and did not produce embryofetal toxicity in pregnant rats following oral administration at doses up to 738 mg/kg/day during the period of organogenesis. The 738 mg/kg/day dose is 177 times the recommended daily human dose of 4.2 mg/kg/day.

Crofelemer was not teratogenic in pregnant rabbits following oral administration at doses up to 400 mg/kg/day during the period of organogenesis. At a dose level of 400 mg/kg/day, which is 96 times the recommended daily human dose of 4.2 mg/kg/day, crofelemer produced an increase in fetal resorptions and abortions compared to controls. However, it is not clear whether these effects are related to the maternal toxicity (decreased body weight and decreased food consumption) observed.

8.2 Lactation

Risk Summary

The Centers for Disease Control and Prevention recommend that HIV-1 infected mothers not breastfeed their infants to avoid risking postnatal transmission of HIV-1.

There are no data on the presence of crofelemer in human milk, the effects on the breastfed infant, or the effects on milk production. Because of the potential for HIV transmission and adverse effects on a breastfed infant, instruct mothers not to breastfeed if they are taking MYTESI.

8.4 Pediatric Use

The safety and effectiveness of MYTESI have not been established in pediatric patients.

8.5 Geriatric Use

Clinical studies with MYTESI did not include sufficient numbers of patients aged 65 and over to determine whether they respond differently than younger patients.

8.6 Use in Patients with Low CD4 Counts and High Viral Loads

No dose modifications are recommended with respect to CD4 cell count and HIV viral load, based on the findings in subgroups of patients defined by CD4 cell count and HIV viral load.

The safety profile of MYTESI was similar in patients with baseline CD4 cell count less than 404 cells/microL (lower limit of normal range) (N=388) and patients with baseline CD4 cell counts greater than or equal to 404 cells/microL (N=289).

The safety profile of crofelemer was similar in patients with baseline HIV viral loads less than 400 copies/mL (N = 412) and patients with baseline HIV viral loads greater than or equal to 400 copies/mL (N = 278).

11 DESCRIPTION

MYTESI (crofelemer) delayed-release tablets is an anti-diarrheal, enteric-coated drug product for oral administration. It contains 125 mg of crofelemer, a botanical drug substance that is derived from the red latex of Croton lechleri Müll. Arg. Crofelemer is an oligomeric proanthocyanidin mixture primarily composed of (+)–catechin, (–)–epicatechin, (+)–gallocatechin, and (–)–epigallocatechin monomer units linked in random sequence, as represented below. The average degree of polymerization for the oligomers ranges between 5 and 7.5, as determined by phloroglucinol degradation.

R = H or OH range n = 3 to 5.5

Inactive ingredients: colloidal silicon dioxide, croscarmellose sodium, magnesium stearate, and microcrystalline cellulose.

Coating ingredients: ethylacrylate and methylacrylate copolymer dispersion, talc, triethyl citrate, and white dispersion which contains xanthan gum, titanium dioxide, propyl paraben, and methyl paraben.

12 CLINICAL PHARMACOLOGY

12.1 Mechanism of Action

Crofelemer is an inhibitor of both the cyclic adenosine monophosphate (cAMP)-stimulated cystic fibrosis transmembrane conductance regulator (CFTR) chloride ion (Cl¯) channel, and the calcium-activated Cl¯ channels (CaCC) at the luminal membrane of enterocytes. The CFTR Cl¯ channel and CaCC regulate Cl¯ and fluid secretion by intestinal epithelial cells. Crofelemer acts by blocking Cl¯ secretion and accompanying high volume water loss in diarrhea, normalizing the flow of Cl¯ and water in the gastrointestinal tract.

12.2 Pharmacodynamics

Consistent with the mechanism of action of crofelemer (i.e., inhibition of CFTR and CaCC in the gastrointestinal lumen), data suggest stool chloride concentrations decreased in patients treated with crofelemer 500 mg four times daily (8-times the recommended daily dosage) (n=25) for four days relative to placebo (n=24); stool chloride concentrations decreased in both African American patients treated with crofelemer (n=3) relative to placebo (n=5) and non-African American patients treated with Mytesi (n=22) relative to placebo (n=19).

Cardiac Electrophysiology

At a dose 10 times the maximum recommended dose, crofelemer does not prolong the QTc interval to any clinically relevant extent.

12.3 Pharmacokinetics

Absorption

The absorption of crofelemer is minimal following oral dosing in healthy adults and HIV–positive patients and concentrations of crofelemer in plasma are below the level of quantitation (50 ng/mL). Therefore, standard pharmacokinetic parameters such as area under the curve, maximum concentration, and half-life cannot be estimated.

Effect of Food

Administration of crofelemer with a high-fat meal was not associated with an increase in systemic exposure of crofelemer in healthy subjects. In the clinical trial, a single 500 mg dose of crofelemer (4-times the recommended dose) was administered one-half hour before the morning and evening meals [see Dosage and Administration (2)].

Drug Interaction Studies

In vitro studies have shown that crofelemer has the potential to inhibit transporters MRP2 and OATP1A2 but not P-gp and BCRP at concentrations expected in the gut.

Due to the minimal absorption of crofelemer, crofelemer is unlikely to inhibit cytochrome P450 isoenzymes 1A2, 2A6, 2B6, 2C9, 2C19, 2D6, and 2E1 systemically.

Nelfinavir, Zidovudine, Lamivudine

Results of a crossover study in healthy subjects showed crofelemer 500 mg administered four times daily (8- times the recommended daily dosage) for five days had no effect on the exposure of zidovudine and nelfinavir when administered as a single dose. A 20% decrease in lamivudine exposure was also observed in the same study but was not considered to be clinically important.

Midazolam

In vitro studies have shown that crofelemer has the potential to inhibit CYP3A4 enzymes at concentrations expected in the gut. The effects of crofelemer on the pharmacokinetics of a single oral dose of 2 mg midazolam, a sensitive CYP3A4 substrate, was evaluated in healthy subjects following crofelemer dosed orally at 500 mg twice daily (4-times the recommended dosage) for six consecutive days. No significant changes in the mean Cmax and AUC were observed for midazolam and its active metabolite, hydroxymidazolam after co- administration with crofelemer compared to that after administration of midazolam alone.

13 NONCLINICAL TOXICOLOGY

13.1 Carcinogenesis, Mutagenesis, Impairment of Fertility

Carcinogenesis

In a 6-month carcinogenicity study in Tg.rasH2 transgenic mice, crofelemer at oral doses up to 125 mg/kg twice a day (250 mg/kg/day) did not produce any drug-related neoplasms in male and female animals. The 250 mg/kg/day dose is about 60 times the recommended clinical dose of 4.2 mg/kg/day (125 mg twice daily).

In a 2-year oral carcinogenicity study in rats, crofelemer at doses up to 100/50 mg/kg twice a day (200/100 mg/kg/day), which is 47.6/23.8 times the recommended clinical dose, did not produce any drug-related neoplastic findings in male and female rats (due to drug-related decreased survival in male rats, 37.5 mg/kg twice daily and 100 mg/kg twice daily doses were reduced to 25 mg/kg twice daily and 50 mg/kg twice daily, respectively, at week 67).

Mutagenesis

Crofelemer was negative in the bacterial reverse mutation assay, chromosomal aberration assay, and rat bone marrow micronucleus assay.

Impairment of Fertility

Crofelemer, at oral doses of up to 738 mg/kg/day (177 times the recommended human daily dose of 125 mg twice daily), had no effects on fertility or reproductive performance of male and female rats.

14 CLINICAL STUDIES

The efficacy of MYTESI was evaluated in a randomized, double-blind, placebo-controlled (one month) and placebo-free (five month), multi-center study. The study enrolled 374 HIV-positive patients on stable anti-retroviral therapy with a history of diarrhea for one month or more. Diarrhea was defined as either persistently loose stools despite regular use of anti-diarrheal medication (e.g., loperamide, diphenoxylate, and bismuth subsalicylate) or one or more watery bowel movements per day without regular anti-diarrheal medicine use.

Patients were excluded if they had a positive gastrointestinal biopsy, gastrointestinal culture, or stool test for multiple bacteria (Salmonella, Shigella, Campylobacter, Yersinia, Mycobacterium), bacterial toxin (Clostridium difficile), ova and parasites (Giardia, Entamoeba, Isospora, Cyclospora, Cryptosporidium, Microsporidium), or viruses (Cytomegalovirus). Patients were also excluded if they had a history of ulcerative colitis, Crohn’s disease, celiac sprue (gluten-enteropathy), chronic pancreatitis, malabsorption, or any other gastrointestinal disease associated with diarrhea.

The study had a two-stage adaptive design. In both stages, patients received placebo for 10 days (screening period) followed by randomization to crofelemer or placebo for 31 days of treatment (double-blind period). Only patients with 1 or more watery bowel movements per day on at least 5 of the last 7 days in the screening period were randomized to the double-blind period. Each stage enrolled patients separately; the dose for the second stage was selected based on an interim analysis of data from the first stage. In the first stage, patients were randomized 1:1:1:1 to one of three crofelemer dosage regimens (125 mg twice daily, or one of two higher dosage regimens) or placebo. In the second stage, patients were randomized 1:1 to MYTESI 125 mg twice daily or placebo. The efficacy analysis was based on results from the double-blind portion of both stages.

Each study stage also had a five month period (placebo-free period) that followed the double-blind period. Patients treated with MYTESI continued the same dose in the placebo-free period. In the first stage, patients that received placebo were re-randomized 1:1:1 to one of the three crofelemer dosage regimens (125 mg twice daily, or one of the two higher dosage regimens) in the placebo-free period. In the second stage, patients that received placebo were treated with MYTESI 125 mg twice daily in the placebo-free period.

The median time since diagnosis of HIV was 12 years. The percentage of patients with a CD4 cell count of less than 404 was 39%. The percentage of patients with a HIV viral load greater than or equal to 1000, 400 to 999, and less than 400 HIV copies/mL was 7%, 3%, and 9%, respectively; the remainder had a viral load that was not detectable. The median time since diarrhea started was 4 years. The median number of daily watery bowel movements was 2.5 per day.

Most patients were male (85%). The percentage of patients that were Caucasian was 46%; the percentage of patients that were African-American was 32%. The median age was 45 years with a range of 21 to 68 years.

In the double-blind period of the study, 136 patients received MYTESI 125 mg twice daily, 101 patients received one of the two higher dosage regimens and 138 patients received placebo. The percentages of patients that completed the double-blind period were 92% in the MYTESI 125 mg group and 94% in the placebo arm.

Most patients received concomitant protease inhibitors during the double-blind period (Table 2). The most frequently used anti-retroviral therapies in the MYTESI 125 mg and placebo groups were tenofovir/emtricitabine, ritonavir, and lopinavir/ritonavir.

Table 2: Concomitant Anti-Retroviral Therapy Used in the Double-Blind Period in Patients with HIV
 | MYTESI 125 mg twice daily (N = 136)n (%) | Placebo N = 138 n (%)
Any antiretroviral therapy | 135 (99) | 134 (97)
Any protease inhibitor | 87 (64) | 97 (70)
Tenofovir/Emtricitabine | 45 (33) | 52 (38)
Ritonavir | 46 (34) | 49 (36)
Lopinavir/Ritonavir | 30 (22) | 40 (29)
Efavirenz/Tenofovir/Emtricitabine | 30 (22) | 21 (15)
Tenofovir disoproxil fumarate | 18 (13) | 14 (10)
Atazanavir sulfate | 19 (14) | 22 (16)
Abacavir w/ lamivudine | 17 (13) | 18 (13)
Darunavir | 19 (14) | 14 (10)
Raltegravir | 16 (12) | 11 (8)
Valaciclovir hydrochloride | 12 (9) | 16 (12)
Fosamprenavir | 12 (9) | 13 (9)
Zidovudine w/lamivudine | 12 (9) | 15 (11)
Lamivudine | 7 (5) | 6 (4)
Nevirapine | 8 (6) | 9 (7)
Atazanavir | 5 (4) | 2 (1)

The primary efficacy endpoint was the proportion of patients with a clinical response, defined as less than or equal to 2 watery bowel movements per week during at least 2 of the 4 weeks of the placebo-controlled phase. Patients who received concomitant anti-diarrheal medications or opiates were counted as clinical non-responders.

A significantly larger proportion of patients in the MYTESI 125 mg twice daily group experienced clinical response compared with patients in the placebo group (18% vs. 8%, 1–sided p < 0.01). In the randomized clinical study, examination of duration of diarrhea, baseline number of daily watery bowel movements, use of protease inhibitors, CD4 cell count and age subgroups did not identify differences in the consistency of the crofelemer treatment effect among these subgroups. There were too few female patients and patients with an HIV viral load > 400 copies/mL to adequately assess differences in effects in these populations. Among race subgroups, there were no differences in the consistency of the crofelemer treatment effect except for the subgroup of African-Americans; crofelemer was less effective in African-Americans than non-African-Americans.

Although the CD4 cell count and HIV viral load did not appear to change over the one month placebo-controlled period, the clinical significance of this finding is unknown because of the short duration of the placebo-controlled period.

Of the 24 clinical responders to MYTESI 125 mg twice daily, 22 entered the placebo-free period; 16 were responding at the end of month 3, and 14 were responding at the end of month 5.

16 HOW SUPPLIED/STORAGE AND HANDLING

MYTESI (crofelemer) 125 mg delayed-release tablets are white, oval tablets printed on one side with 125SLXP.
They are available in the following package size:
Bottles of 60: NDC 70564-802-60
Store at 20°C-25°C (68°F-77°F); excursions permitted between 15°C-30°C (59°F-86°F). See USP Controlled Room Temperature.

17 PATIENT COUNSELING INFORMATION

- Instruct patients that MYTESI tablets may be taken with or without food.
- Instruct patients to swallow MYTESI tablets whole and not to crush or chew the tablets.

Manufactured by Patheon, Inc. for

Napo Pharmaceuticals, Inc., San Francisco, CA 94105

Copyright © Napo Pharmaceuticals, Inc.

US Patent Nos. 7,341,744 and 7,323,195.

NP-367-1 11/2020

70033046

The botanical drug substance of MYTESI is extracted from Croton lechleri (the botanical raw material) that is harvested from the wild in South America.

PACKAGE LABEL

PRINCIPAL DISPLAY PANEL

NDC 70564-802-60
Mytesi™
(crofelemer)
delayed-release tablets
125 mg
Swallow tablet whole. Do not crush or chew.
60 enteric coated tablets Rx only